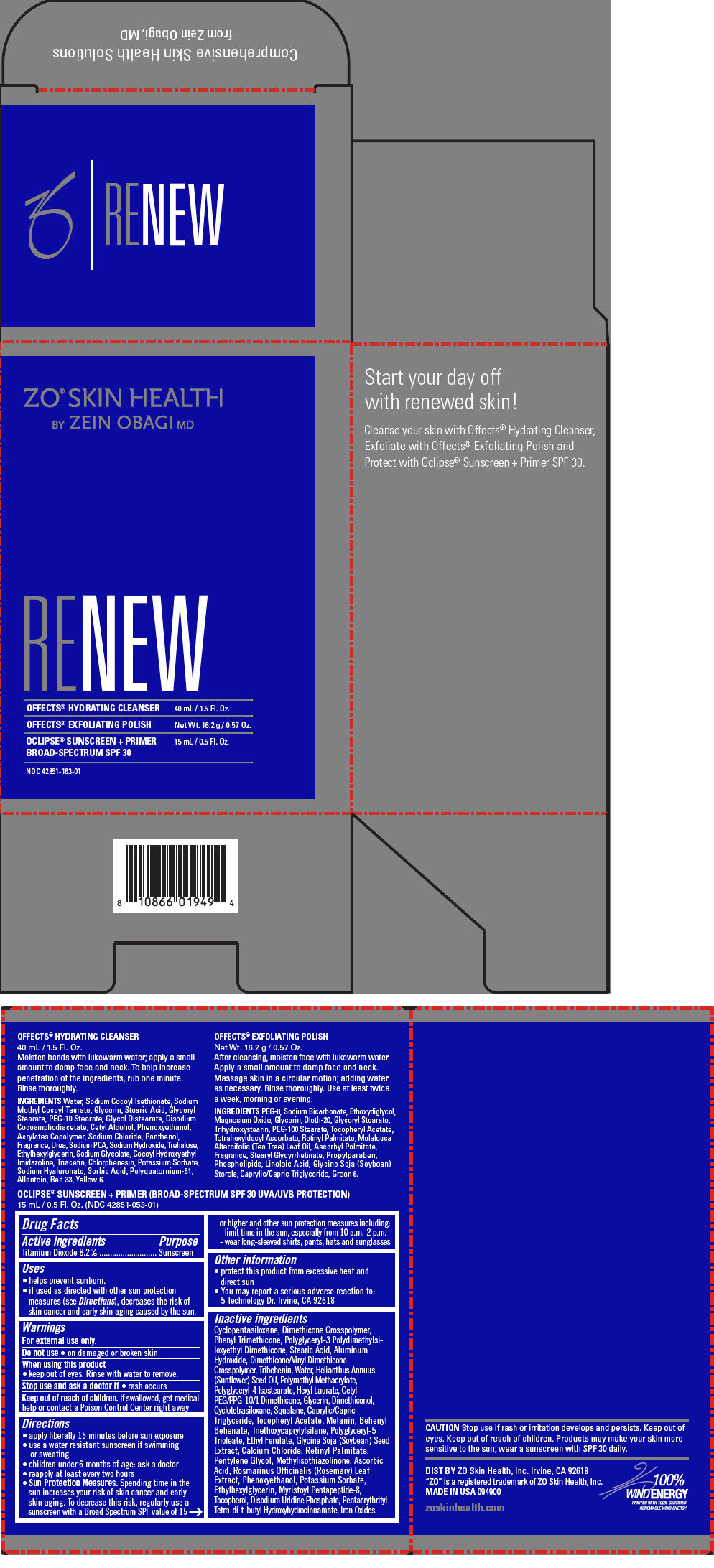 DRUG LABEL: ZO SKIN HEALTH RENEW
NDC: 42851-163 | Form: KIT | Route: TOPICAL
Manufacturer: ZO Skin Health, Inc.
Category: otc | Type: HUMAN OTC DRUG LABEL
Date: 20200617

ACTIVE INGREDIENTS: TITANIUM DIOXIDE 82 mg/1 mL
INACTIVE INGREDIENTS: CYCLOMETHICONE 5; DIMETHICONE CROSSPOLYMER (450000 MPA.S AT 12% IN CYCLOPENTASILOXANE); PHENYL TRIMETHICONE; POLYGLYCERYL-3 POLYDIMETHYLSILOXYETHYL DIMETHICONE (4000 MPA.S); STEARIC ACID; ALUMINUM HYDROXIDE; DIMETHICONE/VINYL DIMETHICONE CROSSPOLYMER (SOFT PARTICLE); TRIBEHENIN; WATER; SUNFLOWER OIL; POLY(METHYL METHACRYLATE; 450000 MW); POLYGLYCERYL-4 ISOSTEARATE; HEXYL LAURATE; CETYL PEG/PPG-10/1 DIMETHICONE (HLB 2); GLYCERIN; DIMETHICONOL (100000 CST); CYCLOMETHICONE 4; SQUALANE; MEDIUM-CHAIN TRIGLYCERIDES; .ALPHA.-TOCOPHEROL ACETATE; MELANIN SYNTHETIC (TYROSINE, PEROXIDE); BEHENYL BEHENATE; TRIETHOXYCAPRYLYLSILANE; ETHYL FERULATE; SOYBEAN; CALCIUM CHLORIDE; VITAMIN A PALMITATE; PENTYLENE GLYCOL; METHYLISOTHIAZOLINONE; ASCORBIC ACID; ROSEMARY; PHENOXYETHANOL; POTASSIUM SORBATE; ETHYLHEXYLGLYCERIN; TOCOPHEROL; URIDINE MONOPHOSPHATE DISODIUM; PENTAERYTHRITOL TETRAKIS(3-(3,5-DI-TERT-BUTYL-4-HYDROXYPHENYL)PROPIONATE); FERRIC OXIDE RED

ZO® SKIN HEALTH RENEW

Drug Facts

Active ingredients

Titanium Dioxide 8.2%

Purpose

Sunscreen

Uses

- helps prevent sunburn.
- if used as directed with other sun protection measures (see Directions), decreases the risk of skin cancer and early skin aging caused by the sun.

Warnings

For external use only.

Do not use

- on damaged or broken skin

When using this product

- keep out of eyes. Rinse with water to remove.

Stop use and ask a doctor if

- rash occurs

Keep out of reach of children. If swallowed, get medical help or contact a Poison Control Center right away

Directions

- apply liberally 15 minutes before sun exposure
- use a water resistant sunscreen if swimming or sweating
- children under 6 months of age: ask a doctor
- reapply at least every two hours
- Sun Protection Measures. Spending time in the sun increases your risk of skin cancer and early skin aging. To decrease this risk, regularly use a sunscreen with a Broad Spectrum SPF value of 15 or higher and other sun protection measures including:
  - limit time in the sun, especially from 10 a.m.-2 p.m.
  - wear long-sleeved shirts, pants, hats and sunglasses

Other information

- protect this product from excessive heat and direct sun
- You may report a serious adverse reaction to: 5 Technology Dr. Irvine, CA 92618

Inactive ingredients

Cyclopentasiloxane, Dimethicone Crosspolymer, Phenyl Trimethicone, Polyglyceryl-3 Polydimethylsiloxyethyl Dimethicone, Stearic Acid, Aluminum Hydroxide, Dimethicone/Vinyl Dimethicone Crosspolymer, Tribehenin, Water, Helianthus Annuus (Sunflower) Seed Oil, Polymethyl Methacrylate, Polyglyceryl-4 Isostearate, Hexyl Laurate, Cetyl PEG/PPG-10/1 Dimethicone, Glycerin, Dimethiconol, Cyclotetrasiloxane, Squalane, Caprylic/Capric Triglyceride, Tocopheryl Acetate, Melanin, Behenyl Behenate, Triethoxycaprylylsilane, Polyglyceryl-5 Trioleate, Ethyl Ferulate, Glycine Soja (Soybean) Seed Extract, Calcium Chloride, Retinyl Palmitate, Pentylene Glycol, Methylisothiazolinone, Ascorbic Acid, Rosmarinus Officinalis (Rosemary) Leaf Extract, Phenoxyethanol, Potassium Sorbate, Ethylhexylglycerin, Myristoyl Pentapeptide-8, Tocopherol, Disodium Uridine Phosphate, Pentaerythrityl Tetra-di-t-butyl Hydroxyhydrocinnamate, Iron Oxides.

DIST BY ZO Skin Health, Inc. Irvine, CA 92618

PRINCIPAL DISPLAY PANEL - Kit Carton

ZO® SKIN HEALTH
BY ZEIN OBAGI MD

RE NEW

OFFECTS® HYDRATING CLEANSER
40 mL / 1.5 Fl. Oz.

OFFECTS® EXFOLIATING POLISH
Net Wt. 16.2 g / 0.57 Oz.

OCLIPSE® SUNSCREEN + PRIMER
BROAD-SPECTRUM SPF 30
15 mL / 0.5 Fl. Oz.

NDC 42851-163-01